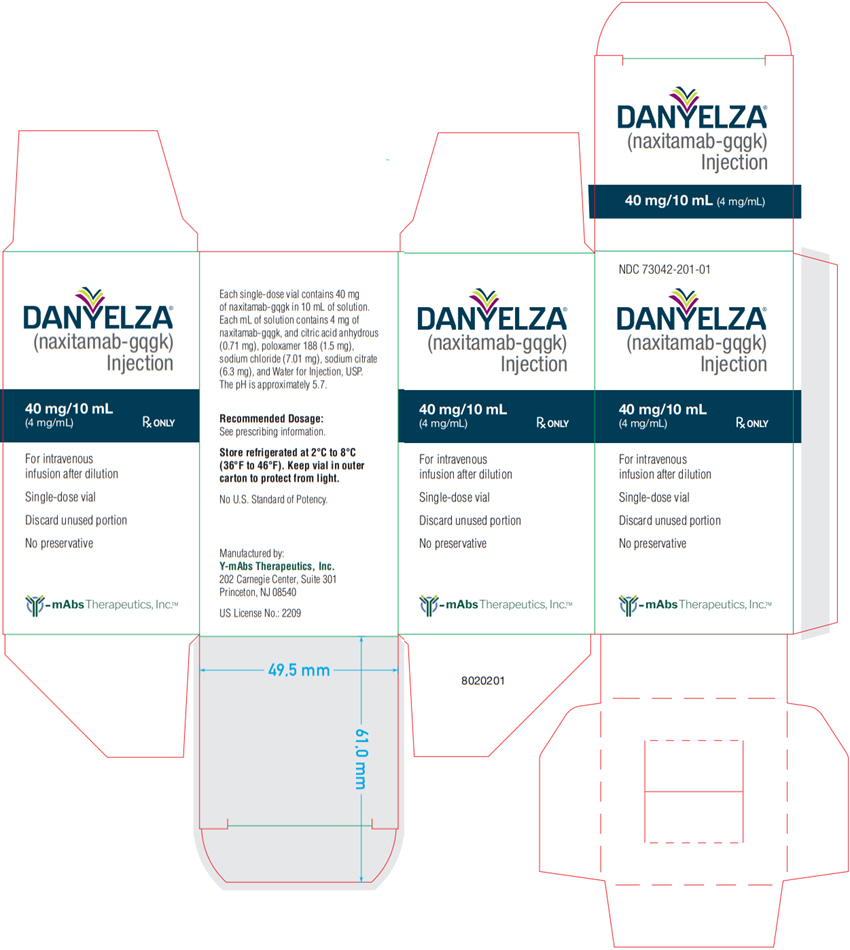 DRUG LABEL: DANYELZA
NDC: 73042-201 | Form: INJECTION
Manufacturer: Y-mAbs Therapeutics, Inc.
Category: prescription | Type: HUMAN PRESCRIPTION DRUG LABEL
Date: 20250903

ACTIVE INGREDIENTS: Naxitamab 40 mg/10 mL
INACTIVE INGREDIENTS: TRISODIUM CITRATE DIHYDRATE; ANHYDROUS CITRIC ACID; SODIUM CHLORIDE; POLOXAMER 188; Water

HIGHLIGHTS OF PRESCRIBING INFORMATION

These highlights do not include all the information needed to use DANYELZA safely and effectively. See full prescribing information for DANYELZA.
DANYELZA® (naxitamab-gqgk) injection, for intravenous use
Initial U.S. Approval: 2020

WARNING: SERIOUS INFUSION-RELATED REACTIONS and NEUROTOXICITY

See full prescribing information for complete boxed warning

- Serious Infusion-Related Reactions: DANYELZA can cause serious infusion reactions, including cardiac arrest, anaphylaxis, hypotension, bronchospasm, and stridor. Premedicate prior to each DANYELZA infusion as recommended. Reduce the rate, interrupt infusion, or permanently discontinue DANYELZA based on severity (2.2, 2.3, 4, 5.1).
- Neurotoxicity: DANYELZA can cause severe neurotoxicity, including severe neuropathic pain, transverse myelitis, and reversible posterior leukoencephalopathy syndrome (RPLS). Premedicate to treat neuropathic pain as recommended. Permanently discontinue DANYELZA based on the adverse reaction and severity (2.2, 2.3, 5.2).

1 INDICATIONS AND USAGE

DANYELZA is a GD2-binding monoclonal antibody indicated, in combination with granulocyte-macrophage colony-stimulating factor (GM-CSF), for the treatment of pediatric patients 1 year of age and older and adult patients with relapsed or refractory high-risk neuroblastoma in the bone or bone marrow who have demonstrated a partial response, minor response, or stable disease to prior therapy.

This indication is approved under accelerated approval based on overall response rate and duration of response. Continued approval for this indication may be contingent upon verification and description of clinical benefit in a confirmatory trial(s). (1)

2 DOSAGE AND ADMINISTRATION

The recommended dosage of DANYELZA is 3 mg/kg/day (up to 150 mg/day), administered as an intravenous infusion after dilution on Days 1, 3, and 5 of each treatment cycle. Treatment cycles are repeated every 4 weeks until complete response or partial response, followed by 5 additional cycles every 4 weeks. Subsequent cycles may be repeated every 8 weeks. Discontinue DANYELZA and GM-CSF for disease progression or unacceptable toxicity. Administer GM-CSF subcutaneously prior to and during each treatment cycle as recommended. (2.1)

3 DOSAGE FORMS AND STRENGTHS

Injection: 40 mg/10 mL (4 mg/mL) in a single-dose vial. (3)

4 CONTRAINDICATIONS

History of severe hypersensitivity reaction to naxitamab-gqgk. (4)

5 WARNINGS AND PRECAUTIONS

- Neurotoxicity: Peripheral neuropathy, neurological disorders of the eye, and prolonged urinary retention have also occurred. Permanently discontinue as recommended. (2.3, 5.2)
- Myocarditis: Withhold, reduce dose, or discontinue based on severity. (2.3, 5.3)
- Hypertension: Monitor blood pressure during and after infusion as recommended. Withhold, reduce infusion rate, or discontinue based on severity. (2.3, 5.4)
- Orthostatic Hypotension: Severe orthostatic hypotension, including cases requiring hospitalization, have occurred. Withhold, reduce dose, or discontinue based on severity. (2.3, 5.5)
- Embryo-Fetal Toxicity: May cause fetal harm. Advise females of reproductive potential of potential risk to a fetus and to use effective contraception. (5.6)

6 ADVERSE REACTIONS

- The most common adverse reactions (≥25%) are infusion-related reaction, pain, tachycardia, vomiting, cough, nausea, diarrhea, decreased appetite, hypertension, fatigue, erythema multiforme, peripheral neuropathy, urticaria, pyrexia, headache, injection site reaction, edema, anxiety, localized edema, and irritability (6.1).
- The most common Grade 3 or 4 laboratory abnormalities (≥5%) are decreased lymphocytes, decreased neutrophils, decreased hemoglobin, decreased platelet count, decreased potassium, increased alanine aminotransferase, decreased glucose, decreased calcium, decreased albumin, decreased sodium, and decreased phosphate (6.1).

To report SUSPECTED ADVERSE REACTIONS, contact Y-mAbs Therapeutics, Inc, at 1-833-339-6227 (1-833-33YMABS), or FDA at 1-800-FDA-1088 or www.fda.gov/medwatch.

8 USE IN SPECIFIC POPULATIONS

Lactation: Advise not to breastfeed. (8.2)

FULL PRESCRIBING INFORMATION

WARNING: SERIOUS INFUSION-RELATED REACTIONS and NEUROTOXICITY

Serious Infusion-Related Reactions

- DANYELZA can cause serious infusion reactions, including cardiac arrest, anaphylaxis, hypotension, bronchospasm, and stridor. Infusion reactions of any Grade occurred in 94-100% of patients. Severe infusion reactions occurred in 32-68% and serious infusion reactions occurred in 4 - 18% of patients in DANYELZA clinical studies [see Warnings and Precautions (5.1)].
- Premedicate prior to each DANYELZA infusion as recommended and monitor patients for at least 2 hours following completion of each infusion. Reduce the rate, interrupt infusion, or permanently discontinue DANYELZA based on severity [see Dosage and Administration (2.2, 2.3), Contraindications (4), and Warnings and Precautions (5.1)].

Neurotoxicity

- DANYELZA can cause severe neurotoxicity, including severe neuropathic pain, transverse myelitis and reversible posterior leukoencephalopathy syndrome (RPLS). Pain of any Grade occurred in 94-100% of patients in DANYELZA clinical studies [see Warnings and Precautions (5.2)].
- Premedicate to treat neuropathic pain as recommended. Permanently discontinue DANYELZA based on the adverse reaction and severity [see Dosage and Administration (2.2, 2.3) and Warnings and Precautions (5.2)].

1 INDICATIONS AND USAGE

DANYELZA is indicated, in combination with granulocyte-macrophage colony-stimulating factor (GM-CSF), for the treatment of pediatric patients 1 year of age and older and adult patients with relapsed or refractory high-risk neuroblastoma in the bone or bone marrow who have demonstrated a partial response, minor response, or stable disease to prior therapy.

This indication is approved under accelerated approval based on overall response rate and duration of response [see Clinical Studies (14)]. Continued approval for this indication may be contingent upon verification and description of clinical benefit in a confirmatory trial(s).

2 DOSAGE AND ADMINISTRATION

2.1 Recommended Dosage

The recommended dosage of DANYELZA is 3 mg/kg/day (up to 150 mg/day) on Days 1, 3, and 5 of each treatment cycle, administered as an intravenous infusion after dilution [see Dosage and Administration (2.4 and 2.5)] in combination with GM-CSF subcutaneously as shown in Table 1. Refer to the GM-CSF Prescribing Information for recommended dosing information.

Treatment cycles are repeated every 4 weeks until complete response or partial response, followed by 5 additional cycles every 4 weeks. Subsequent cycles may be repeated every 8 weeks. Discontinue DANYELZA and GM-CSF for disease progression or unacceptable toxicity.

Administer pre-infusion medications and supportive treatment, as appropriate, during infusion. [see Dosage and Administration (2.2)]

The recommended dosage regimen for each treatment cycle is described below and in Table 1:

- Days -4 to 0: administer GM-CSF 250 µg/m^2/day by subcutaneous injection, beginning 5 days prior to DANYELZA infusion.
- Days 1 to 5: administer GM-CSF 500 µg/m^2/day by subcutaneous injection. Administer at least 1 hour prior to DANYELZA administration on Days 1, 3, and 5.
- Days, 1, 3, and 5: administer DANYELZA 3 mg/kg/day (up to 150 mg/day) by intravenous infusion.

Table 1 Dose and Schedule of GM-CSF and DANYELZA Within One Treatment Cycle
Day |  | -4 | -3 | -2 | -1 | 0 | 1 | 2 | 3 | 4 | 5
Subcutaneous GM-CSF |  | 250 µg/m^2/day |  |  |  |  | 500 µg/m^2/day
Intravenous DANYELZA |  |  |  |  |  |  | 3 mg/kg/day |  | 3 mg/kg/day |  | 3 mg/kg/day

Missed Dose

If a DANYELZA dose is missed, administer the missed dose the following week by Day 10. Administer GM-CSF 500 µg /m^2/day on the first day of the DANYELZA infusion, and on the day before and on the day of the second and third infusion, respectively (i.e. a total of 5 days with 500 µg /m^2/day).

2.2 Premedications and Supportive Medications

Pain Management Prior to and During Infusion [see Warnings and Precautions (5.2)]:

- Five days prior to the first infusion of DANYELZA in each cycle, initiate a 12-day course (Day -4 through Day 7) of prophylactic medication for neuropathic pain, such as gabapentin.
- Administer oral opioids 45-60 minutes prior to initiation of each DANYELZA infusion and additional intravenous opioids as needed for breakthrough pain during the infusion.
- Consider use of ketamine for pain that is not adequately controlled by opioids.

Premedication: Reduce Risk of Infusion-Related Reactions and Nausea/Vomiting [see Warnings and Precautions (5.1) and Adverse Reactions (6.1)].

- Administer intravenous corticosteroids (e.g. methylprednisolone 2 mg/kg with maximum dose of 80 mg or equivalent corticosteroid dose) 30 minutes to 2 hours prior to the first infusion of DANYELZA. Administer corticosteroid premedication for subsequent infusions if a severe infusion reaction occurred with the previous infusion or during the previous cycle.
- Administer an antihistamine, an H2 antagonist, acetaminophen and an antiemetic 30 minutes prior to each infusion.

2.3 Dosage Modifications for Adverse Reactions

The recommended dosage modifications for DANYELZA for adverse reactions are presented in Table 2.

Table 2. Recommended DANYELZA Dosage Modifications for Adverse Reactions
Adverse Reaction | Severity [Based on Common Terminology Criteria for Adverse Events (CTCAE) v 5.0] | Dosage Modifications
Infusion-related reactions [see Warnings and Precautions (5.1)] | Grade 2 Defined as: Therapy or infusion interruption indicated but responds promptly to symptomatic treatment (e.g., antihistamines, NSAIDS, narcotics, IV fluids); prophylactic medications indicated for ≤24 hours | - Reduce DANYELZA infusion rate to 50% of previous rate and monitor closely until recovery to Grade ≤ 1. - Increase infusion rate gradually to rate prior to the event as tolerated.
Infusion-related reactions [see Warnings and Precautions (5.1)] | Grade 3 Defined as: Prolonged (e.g., not rapidly responsive to symptomatic medication and/or brief interruption of infusion); recurrence of symptoms following initial improvement; hospitalization indicated for clinical sequelae | - Immediately interrupt DANYELZA infusion and monitor closely until recovery to Grade ≤ 2. - Resume infusion at 50% of the rate prior to the event and increase infusion rate gradually to infusion rate prior to the event as tolerated. - Permanently discontinue DANYELZA in patients not responding to medical intervention.
Infusion-related reactions [see Warnings and Precautions (5.1)] | Grade 4 infusion-related reactions Defined as: Life-threatening consequences: urgent intervention indicated or Grade 3 or 4 anaphylaxis | - Permanently discontinue DANYELZA.
Pain [see Warnings and Precautions (5.2)] | Grade 3 unresponsive to maximum supportive measures | - Permanently discontinue DANYELZA.
Reversible posterior leukoencephalopathy syndrome (RPLS) [see Warnings and Precautions (5.2)] | All Grades | - Permanently discontinue DANYELZA.
Transverse myelitis [see Warnings and Precautions (5.2)] | All Grades | - Permanently discontinue DANYELZA.
Peripheral neuropathy [see Warnings and Precautions (5.2)] | Motor neuropathy: Grade 2 or greater or Sensory neuropathy: Grade 3 or 4 | - Permanently discontinue DANYELZA.
Neurological disorders of the eye [see Warnings and Precautions (5.2)] | Grade 2 to 4 resulting in decreased visual acuity or limiting activities of daily living | - Withhold DANYELZA until resolution. - If resolved resume DANYELZA at 50% of the prior dose; if tolerated without recurrence of symptoms, gradually increase DANYELZA to dose prior to onset of symptoms. - Permanently discontinue DANYELZA if not resolved within 2 weeks or upon recurrence.
Neurological disorders of the eye [see Warnings and Precautions (5.2)] | Subtotal or total vision loss | - Permanently discontinue DANYELZA.
Prolonged urinary retention [see Warnings and Precautions (5.2)] | Persisting following discontinuation of opioids | - Permanently discontinue DANYELZA.
Myocarditis [see Warnings and Precautions (5.3)] | Grade 2 or 3 | - Withhold, reduce dose, or permanently discontinue DANYELZA treatment based on severity and duration.
Myocarditis [see Warnings and Precautions (5.3)] | Grade 4 | - Permanently discontinue DANYELZA.
Hypertension [see Warnings and Precautions (5.4)] | Grade 3 | - Withhold DANYELZA or pause infusion until recovery to ≤ Grade 2. - Resume infusion at 50% of prior rate; if tolerated without recurrence of symptoms, gradually increase DANYELZA to rate prior to onset of symptoms. - Permanently discontinue DANYELZA in patients not responding to medical intervention.
Hypertension [see Warnings and Precautions (5.4)] | Grade 4 | - Permanently discontinue DANYELZA.
Orthostatic hypotension [see Warnings and precautions (5.5)] | All grades | - Withhold DANYELZA until recovery to Grade ≤ 1. - If resolved within 1 week, restart DANYELZA at 50% of the prior dose; if tolerated without recurrence of symptoms after completion of next cycle, resume to recommended dose for subsequent cycles. - If not resolved within 1 week, permanently discontinue DANYELZA.
Other Adverse Reactions [see Adverse Reactions (6.1)] | Grade 3 | - Withhold DANYELZA until recovery to Grade ≤ 2. - If resolved to Grade ≤ 2 resume DANYELZA at same rate. - Permanently discontinue DANYELZA if not resolved to Grade ≤2 within 2 weeks.
Other Adverse Reactions [see Adverse Reactions (6.1)] | Grade 4 | - Permanently discontinue DANYELZA.

2.4 Preparation

- Use appropriate aseptic technique.
- Visually inspect vial for particulate matter and discoloration prior to administration. Discard vial if solution is discolored, cloudy, or contains particulate matter.
- Add appropriate quantities of 5% Albumin (Human), USP and 0.9% Sodium Chloride Injection, USP to an empty, sterile intravenous infusion bag large enough to hold the volume needed for the relevant dose as indicated in Table 3. Allow for 5-10 minutes of passive mixing.
- Withdraw the required dose of DANYELZA and inject into the infusion bag containing the 5% Albumin (Human), USP and 0.9% Sodium Chloride Injection, USP. Discard any unused portion of DANYELZA left in the vial.

Preparation instructions for DANYELZA are described in Table 3.

Table 3. Preparation of DANYELZA, 4 mg/mL
DANYELZA dose (mg) | DANYELZA volume (mL) | Volume of 5% Albumin (Human), USP (mL) | Total infusion volume achieved by adding sufficient 0.9% Sodium Chloride Injection, USP (mL) | Final concentration of prepared DANYELZA infusion (mg/mL)
≤ 80 | ≤ 20 | 10 | 50 | ≤ 1.6
81 to 120 | > 20 to 30 | 15 | 75 | 1.1 to 1.6
121 to 150 | > 30 to 37.5 | 20 | 100 | 1.2 to 1.5

If not used immediately, store the diluted DANYELZA infusion solution at room temperature (15°C to 25°C [59ºF to 77ºF]) for up to 8 hours or refrigerate (2°C to 8°C [36°F to 46°F]) for up to 24 hours. Once removed from refrigeration, initiate infusion within 8 hours.

2.5 Administration

- Administer DANYELZA as a diluted intravenous infusion as recommended. Do not administer DANYELZA as an intravenous push or bolus [see Dosage and Administration (2.4)].
- For the first infusion (Cycle 1, Day 1), administer DANYELZA intravenously over 60 minutes. For subsequent infusions, administer DANYELZA intravenously over 30 to 60 minutes, as tolerated. [see Dosage and Administration (2.1, 2.3)].
- Observe patients for a minimum of 2 hours following each infusion.

3 DOSAGE FORMS AND STRENGTHS

Injection: 40 mg/10 mL (4 mg/mL) clear to slightly opalescent and colorless to slightly yellow solution in a single-dose vial.

4 CONTRAINDICATIONS

DANYELZA is contraindicated in patients with a history of severe hypersensitivity reaction to naxitamab-gqgk. Reactions have included anaphylaxis [see Warnings and Precautions (5.1)].

5 WARNINGS AND PRECAUTIONS

5.1 Serious Infusion-Related Reactions

DANYELZA can cause serious infusion reactions requiring urgent intervention including fluid resuscitation, administration of bronchodilators and corticosteroids, intensive care unit admission, infusion rate reduction or interruption of DANYELZA infusion. Infusion-related reactions included hypotension, bronchospasm, hypoxia, and stridor [see Adverse Reactions (6.1)].

Serious infusion-related reactions occurred in 4% of patients in Study 201 and in 18% of patients in Study 12-230. Infusion-related reactions of any Grade occurred in 100% of patients in Study 201 and 94% of patients in Study 12-230. Hypotension of any grade occurred in 100% of patients in Study 201 and 89% of patients in Study 12-230.

In Study 201, 68% of patients experienced Grade 3 or 4 infusion reactions; and in Study 12-230, 32% of patients experienced Grade 3 or 4 infusion reactions. Anaphylaxis occurred in 12% of patients and 2 patients (8%) permanently discontinued DANYELZA due to anaphylaxis in Study 201. One patient in Study 12-230 (1.4%) experienced a Grade 4 cardiac arrest 1.5 hours following completion of DANYELZA infusion.

In Study 201, infusion reactions generally occurred within 24 hours of completing a DANYELZA infusion, most often within 30 minutes of initiation. Infusion reactions were most frequent during the first infusion of DANYELZA in each cycle. Eighty percent of patients required reduction in infusion rate and 80% of patients had an infusion interrupted for at least one infusion-related reaction.

Caution is advised in patients with pre-existing cardiac disease, as this may exacerbate the risk of severe hypotension.

Premedicate with an antihistamine, acetaminophen, an H2 antagonist and corticosteroid as recommended [see Dosage and Administration (2.2)]. Monitor patients closely for signs and symptoms of infusion reactions during and for at least 2 hours following completion of each DANYELZA infusion in a setting where cardiopulmonary resuscitation medication and equipment are available.

Reduce the rate, interrupt infusion, or permanently discontinue DANYELZA based on severity and institute appropriate medical management as needed [see Dosage and Administration (2.3) and Contraindications (4)].

5.2 Neurotoxicity

DANYELZA can cause severe neurotoxicity, including severe neuropathic pain, transverse myelitis, and reversible posterior leukoencephalopathy syndrome.

Pain

Pain, including abdominal pain, bone pain, neck pain, and extremity pain, occurred in 100% of patients in Study 201 and 94% of patients in Study 12-230. Grade 3 pain occurred in 72% of patients in Study 201. One patient in Study 201 (4%) required interruption of an infusion due to pain. Pain typically began during the infusion of DANYELZA and lasted a median of less than one day in Study 201 (range less than one day and up to 62 days) [see Adverse Reactions (6.1)].

Premedicate with drugs that treat neuropathic pain (e.g., gabapentin) and oral opioids. Administer intravenous opioids as needed for breakthrough pain [see Dosage and Administration (2.2)]. Permanently discontinue DANYELZA based on severity [see Dosage and Administration (2.3)].

Transverse Myelitis

Transverse myelitis has occurred with DANYELZA. Permanently discontinue DANYELZA in patients who develop transverse myelitis [see Dosage and Administration (2.3)].

Reversible Posterior Leukoencephalopathy Syndrome (RPLS)

Reversible posterior leukoencephalopathy syndrome (RPLS) (also known as posterior reversible encephalopathy syndrome or PRES) occurred in 2 (2.8%) patients in Study 12-230. Events occurred 2 and 7 days following completion of the first cycle of DANYELZA. Monitor blood pressure during and following DANYELZA infusion and assess for neurologic symptoms [see Warnings and Precautions (5.3)]. Permanently discontinue DANYELZA in case of symptomatic RPLS [see Dosage and Administration (2.3) and Adverse Reactions (6.1)].

Peripheral Neuropathy

Peripheral neuropathy, including peripheral sensory neuropathy, peripheral motor neuropathy, paresthesia, and neuralgia, occurred in 32% of patients in Study 201 and in 25% of patients in Study 12-230. Most signs and symptoms of neuropathy began on the day of the infusion and neuropathy lasted a median of 5.5 days (range 0 to 22 days) in Study 201 and 0 days (range 0 to 22 days) in Study 12-230 [see Adverse Reactions (6.1)].

Permanently discontinue DANYELZA based on severity [see Dosage and Administration (2.3)].

Neurological Disorders of the Eye

Neurological disorders of the eye including unequal pupils, blurred vision, accommodation disorder, mydriasis, visual impairment, and photophobia occurred in 24% of patients in Study 201 and 19% of patients in Study 12-230. Neurological disorders of the eye lasted a median of 17 days (range 0 to 84 days) in Study 201 with two patients (8%) experiencing an event that had not resolved at the time of data cutoff, and a median of 1 day (range less than one day to 21 days) in Study 12-230. Permanently discontinue DANYELZA based on severity [see Dosage and Administration (2.3) and Adverse Reactions (6.1)].

Prolonged Urinary Retention

Urinary retention occurred in 1 (4%) patient in Study 201 and in 3 patients (4%) in Study 12-230. All events in both studies occurred on the day of an infusion of DANYELZA and lasted between 0 and 24 days. Permanently discontinue DANYELZA in patients with urinary retention that does not resolve following discontinuation of opioids [see Dosage and Administration (2.3) and Adverse Reactions (6.1)].

5.3 Myocarditis

Myocarditis has occurred in adolescent patients receiving DANYELZA in clinical trials and expanded access programs. Myocarditis occurred within days of receiving DANYELZA requiring drug interruption. Monitor for signs and symptoms of myocarditis during treatment with DANYELZA. Withhold, reduce the dose, or permanently discontinue DANYELZA based on severity [see Dosage and Administration (2.3)].

5.4 Hypertension

Hypertension occurred in 44% of patients in Study 201 and 28% of patients in Study 12-230 who received DANYELZA. Grade 3 or 4 hypertension occurred in 4% of patients in Study 201 and 7% of patients in Study 12-230. Four patients (6%) in Study 12-230 permanently discontinued DANYELZA due to hypertension. In both studies, most events occurred on the day of DANYELZA infusion and occurred up to 9 days following an infusion of DANYELZA.

Do not initiate DANYELZA in patients with uncontrolled hypertension. Monitor blood pressure during infusion, and at least daily on Days 1 to 8 of each cycle of DANYELZA and evaluate for complications of hypertension including RPLS [see Warnings and Precautions (5.2)]. Interrupt DANYELZA infusion and resume at a reduced rate, or permanently discontinue DANYELZA based on the severity [see Dosage and Administration (2.3) and Adverse Reactions (6.1)].

5.5 Orthostatic Hypotension

Orthostatic hypotension has occurred in patients receiving DANYELZA in clinical trials and expanded access programs. Severe orthostatic hypotension, including cases requiring hospitalization, have occurred. Cases occurred within hours to 6 days of DANYELZA infusions in any cycle.

In patients with symptoms of orthostatic hypotension, monitor postural blood pressure prior to initiating treatment with DANYELZA and as clinically indicated with subsequent dosing. Withhold, reduce dose, or permanently discontinue DANYELZA based on severity [see Dosage and Administration (2.3)].

5.6 Embryo-Fetal Toxicity

Based on its mechanism of action, DANYELZA may cause fetal harm when administered to a pregnant woman. Advise females of reproductive potential, including pregnant women, of the potential risk to a fetus. Advise females of reproductive potential to use effective contraceptive during treatment with DANYELZA and for two months after the last dose. [see Use in Specific Populations (8.1, 8.3)].

6 ADVERSE REACTIONS

The following clinically significant adverse reactions are also described elsewhere in the labeling:

- Serious Infusion-Related Reactions [see Warnings and Precautions (5.1)]
- Neurotoxicity [see Warnings and Precautions (5.2)]
- Myocarditis [see Warnings and Precautions (5.3)]
- Hypertension [see Warnings and Precautions (5.4)]
- Orthostatic Hypotension [see Warnings and Precautions (5.5)]

6.1 Clinical Trials Experience

Because clinical trials are conducted under widely varying conditions, adverse reaction rates observed in the clinical trials of a drug cannot be directly compared to rates in the clinical trials of another drug and may not reflect the rates observed in practice.

The safety of DANYELZA in combination with GM-CSF was evaluated in patients with refractory or relapsed high-risk neuroblastoma in bone or bone marrow who had demonstrated a partial response, minor response, or stable disease following initial or subsequent therapy, and in patients who were in second complete remission, from two open-label, single arm studies, Study 201 (n=25) and Study 12-230 (n=72). Patients received DANYELZA 9 mg/kg/cycle administered as three separate intravenous infusions of 3 mg/kg (Day 1, 3 and 5) in the first week of each cycle. Patients also received GM-CSF 250 µg/m^2/day subcutaneously on Days -4 to 0 and GM-CSF 500 µg/m^2/day subcutaneously on Days 1 to 5 [see Clinical Studies (14)].

The most common adverse reactions in Studies 201 and 12-230 (≥25% in either study) were infusion-related reaction, pain, tachycardia, vomiting, cough, nausea, diarrhea, decreased appetite, hypertension, fatigue, erythema multiforme, peripheral neuropathy, urticaria, pyrexia, headache, injection site reaction, edema, anxiety, localized edema and irritability. The most common Grade 3 or 4 laboratory abnormalities (≥5% in either study) were decreased lymphocytes, decreased neutrophils, decreased hemoglobin, decreased platelet count, decreased potassium, increased alanine aminotransferase, decreased glucose, decreased calcium, decreased albumin, decreased sodium and decreased phosphate.

Study 201

In Study 201, among 25 patients who received DANYELZA in combination with GM-CSF, 12% were exposed for 6 months or longer and none were exposed for greater than one year.

Serious adverse reactions occurred in 32% of patients who received DANYELZA in combination with GM-CSF. Serious adverse reactions in more than one patient included anaphylactic reaction (12%) and pain (8%). Permanent discontinuation of DANYELZA due to an adverse reaction occurred in 12% of patients. Adverse reactions resulting in permanent discontinuation of DANYELZA included anaphylactic reaction (8%) and respiratory depression (4%).

Dosage interruptions of DANYELZA due to an adverse reaction occurred in 84% of patients. Adverse reactions requiring dosage interruption in > 10% of patients included hypotension and bronchospasm.

Table 4 summarizes adverse reactions in Study 201.

Table 4. Adverse Reactions (>10%) in Patients with Refractory or Relapsed High-Risk Neuroblastoma in Bone or Bone Marrow Who Received DANYELZA with GM-CSF in Study 201
 | DANYELZA with GM-CSF [Adverse reactions were graded using CTCAE version 4.0.] (n=25)
Adverse Reaction | All Grades (%) | Grade 3 or 4 (%)
Body system
General disorders and administration site conditions
Pain [Pain includes pain, abdominal pain, pain in extremity, bone pain, neck pain, back pain, and musculoskeletal pain.] | 100 | 72
Infusion-related reaction [Infusion-related reaction includes hypotension, bronchospasm, flushing, wheezing, stridor, urticaria, dyspnea, pyrexia, infusion-related reaction, face edema, edema mouth, tongue edema, lip edema, respiratory tract edema, chills, hypoxia, pruritis and rash occurring on the day of infusion or the day following an infusion.] | 100 | 68
Edema | 28 | 0
Fatigue [Fatigue includes fatigue, asthenia.] | 28 | 0
Pyrexia [Pyrexia not occurring on the day of infusion or the day following an infusion] | 28 | 0
Respiratory, thoracic and mediastinal disorders
Cough | 60 | 0
Rhinorrhea | 24 | 0
Vascular disorders
Hypertension | 44 | 4
Gastrointestinal disorders
Vomiting | 60 | 4
Diarrhea | 56 | 8
Nausea | 56 | 0
Skin and subcutaneous tissue disorders
Urticaria [Urticaria, not occurring on the day of infusion or the day following an infusion] | 32 | 4
Cardiac disorders
Tachycardia [Tachycardia includes sinus tachycardia and tachycardia] | 84 | 4
Nervous system disorders
Peripheral neuropathy [Peripheral neuropathy includes peripheral sensory neuropathy, paresthesia, neuralgia.] | 32 | 0
Headache | 28 | 8
Depressed level of consciousness | 24 | 16
Eye disorders
Neurological disorders of the eye [Neurological disorders of the eye includes unequal pupils, blurred vision, and mydriasis.] | 24 | 0
Immune system disorders
Anaphylactic reaction | 12 | 12
Metabolism and nutrition disorders
Decreased appetite | 16 | 0
Infections and infestations
Influenza | 12 | 0
Rhinovirus infection | 12 | 0
Upper respiratory tract infection | 12 | 0
Investigations
Weight decreased | 12 | 0
Psychiatric disorders
Anxiety | 12 | 0

Clinically relevant adverse reactions occurring in ≤10% of patients who received DANYELZA with GM-CSF included peripheral edema (8%).

Table 5 summarizes the laboratory abnormalities in Study 201.

Table 5. Selected Laboratory Abnormalities (>20%) Worsening from Baseline in Patients with Refractory or Relapsed High-Risk Neuroblastoma in Bone or Bone Marrow Who Received DANYELZA with GM-CSF in Study 201
Laboratory Abnormality | DANYELZA with GM-CSF [The table presents laboratory parameters with available grading according to CTCAE version 4.0. Baseline evaluation was the last non-missing value prior to first DANYELZA dosing. Each test incidence is based on the number of patients who had both a baseline value and at least one on-study laboratory measurement (range: 23 to 24 patients).] n=25
Laboratory Abnormality | All Grades (%) | Grade 3 or 4 (%)
Chemistry
Decreased potassium | 63 | 8
Decreased albumin | 50 | 0
Increased alanine aminotransferase | 42 | 8
Decreased sodium | 29 | 0
Hematology
Decreased lymphocytes | 74 | 30
Decreased platelet count | 65 | 17
Decreased neutrophils | 61 | 39
Decreased hemoglobin | 48 | 4

Study 12-230

In Study 12-230, among 72 patients who received DANYELZA in combination with GM-CSF, 32% were exposed for 6 months or longer and 8% were exposed for greater than one year.

Serious adverse reactions occurred in 40% of patients who received DANYELZA in combination with GM-CSF. Serious adverse reactions in > 5% of patients included hypertension (14%), hypotension (11%), and pyrexia (8%). Permanent discontinuation of DANYELZA due to an adverse reaction occurred in 8% of patients. Four (6%) patients permanently discontinued DANYELZA due to hypertension and one (1.4%) patient discontinued due to RPLS.

Table 6 summarizes adverse reactions in Study 12-230.

Table 6. Adverse Reactions (>10%) in Patients with Refractory or Relapsed High-Risk Neuroblastoma in Bone or Bone Marrow Who Received DANYELZA with GM-CSF in Study 12-230
 | DANYELZA with GM-CSF [In Study 12-230, all adverse reactions occurring in Cycle 1 and 2, and adverse reactions of ≥ Grade 3 severity occurring in subsequent cycles were reported. In the dose finding phase, Grade 2 unexpected adverse reactions were also reported for Cycles 3 and later.] , [Adverse reactions were graded using CTCAE version 4.0.] (n=72)
Adverse Reaction | All Grades (%) | Grade 3 or 4 (%)
Body system
General disorders and administration site conditions
Infusion-related reaction [Infusion-related reaction includes hypotension, bronchospasm, flushing, wheezing, stridor, urticaria, dyspnea, pyrexia, face edema, periorbital edema, lip swelling, swollen tongue, chills, hypoxia, pruritis, rash maculopapular and rash erythematous occurring on the day of infusion or the day following an infusion.] | 94 | 32
Pain [Pain includes pain, abdominal pain, pain in extremity, bone pain, neck pain, back pain, non-cardiac chest pain, flank pain, and musculoskeletal pain.] | 94 | 2.8
Fatigue [Fatigue includes fatigue, asthenia.] | 44 | 0
Injection site reaction | 28 | 0
Localized edema | 25 | 0
Pyrexia [Pyrexia not occurring on the day of infusion or the day following an infusion.] | 11 | 0
Vascular disorders
Hypertension | 28 | 7
Gastrointestinal disorders
Vomiting | 63 | 2.8
Nausea | 57 | 1.4
Diarrhea | 50 | 4.2
Constipation | 15 | 0
Skin and subcutaneous tissue disorders
Erythema multiforme | 33 | 0
Hyperhidrosis | 17 | 0
Erythema | 11 | 0
Respiratory, thoracic and mediastinal disorders
Cough | 57 | 0
Oropharyngeal pain | 15 | 0
Rhinorrhea | 15 | 0
Nervous system disorders
Peripheral neuropathy [Peripheral neuropathy includes peripheral sensory neuropathy, peripheral motor neuropathy, paresthesia, neuralgia.] | 25 | 0
Headache | 18 | 0
Lethargy | 14 | 0
Metabolism and nutrition disorders
Decreased appetite | 53 | 4.2
Cardiac disorders
Sinus tachycardia | 44 | 1.4
Psychiatric disorders
Anxiety | 26 | 0
Irritability | 25 | 0
Investigations
Breath sounds abnormal | 15 | 0
Injury and procedural complications
Contusion | 15 | 0
Infections and infestations
Rhinovirus infection | 14 | 0
Enterovirus infection | 13 | 0
Eye Disorders
Neurological disorders of the eye [Neurological disorders of the eye includes unequal pupils, blurred vision, accommodation disorder, visual impairment and photophobia.] | 19 | 0

Clinically relevant adverse reactions in ≤10% of patients who received DANYELZA with GM-CSF included apnea (4.2%), hypopnea (2.8%), generalized edema (2.8%), peripheral edema (8.3%), and device related infection (4.2%).

Table 7 summarizes the laboratory abnormalities in Study 12-230.

Table 7. Selected Laboratory Abnormalities (>20%) Worsening from Baseline in Patients with Refractory or Relapsed High-Risk Neuroblastoma in Bone or Bone Marrow Who Received DANYELZA with GM-CSF in Study 12-230
Laboratory Abnormality | DANYELZA with GM-CSF [The table presents laboratory parameters with available grading according to CTCAE version 4.0. Baseline evaluation was the last non-missing value prior to first DANYELZA dosing. Each test incidence is based on the number of patients who had both a baseline value and at least one on-study laboratory measurement (range 19 to 72 patients).] n=72
Laboratory Abnormality | All Grades (%) | Grade 3 or 4 (%)
Chemistry
Increased glucose | 74 | 0
Decreased albumin | 68 | 7
Decreased calcium | 64 | 8
Increased alanine aminotransferase | 55 | 9
Decreased magnesium | 54 | 0
Increased aspartate aminotransferase | 49 | 4
Decreased phosphate | 47 | 5
Decreased potassium | 47 | 32
Decreased sodium | 38 | 6
Decreased glucose | 29 | 8
Hematology
Decreased lymphocytes | 79 | 56
Decreased hemoglobin | 76 | 42
Decreased neutrophils | 72 | 46
Decreased platelets | 71 | 40

6.2 Immunogenicity

As with all therapeutic proteins, there is a potential for immunogenicity. The detection of anti-drug antibody formation is highly dependent on the sensitivity and specificity of the assay. Additionally, the observed incidence of anti-drug antibody (including neutralizing antibody) positivity in an assay may be influenced by several factors, including assay methodology, sample handling, timing of sample collection, concomitant medications, and underlying disease. For these reasons, comparison of the incidence of anti-drug antibodies in the studies described below with the incidence of anti-drug antibodies in other studies or to other naxitamab products may be misleading.

In Study 201, 2 of 24 (8%) patients tested positive for anti-drug antibodies (ADA) after treatment with DANYELZA.

In Study 12-230, 27 of 117 patients (23%) tested positive for ADA after treatment with DANYELZA by an assay that was not fully validated; therefore, the incidence of ADA may not be reliable.

6.3 Postmarketing Experience/Spontaneous Reports

The following adverse reactions have been identified during expanded access and post-approval use of DANYELZA. Because these reactions are reported voluntarily from a population of uncertain size, it is not always possible to reliably estimate their frequency or establish a causal relationship to drug exposure.

Neurological: Orthostatic hypotension, Transverse myelitis

Cardiac disorders: Myocarditis

8 USE IN SPECIFIC POPULATIONS

8.1 Pregnancy

Risk Summary

Based on its mechanism of action, DANYELZA may cause fetal harm when administered to pregnant women [see Clinical Pharmacology (12.1)]. There are no available data on the use of DANYELZA in pregnant women and no animal reproduction studies have been conducted with DANYELZA. IgG1 monoclonal antibodies are transported across the placenta in a linear fashion as pregnancy progresses, with the largest amount transferred during the third trimester. Advise pregnant women of potential risk to a fetus.

In the U.S. general population, the estimated background risk of major birth defects and miscarriage in clinically recognized pregnancies is 2% to 4% and 15% to 20%, respectively.

8.2 Lactation

Risk Summary

There are no data on the presence of naxitamab-gqgk in human milk or its effects on the breastfed child, or on milk production, however, human IgG is present in human milk. Because of the potential for serious adverse reactions in a breastfed child from DANYELZA, advise women not to breastfeed during treatment and for 2 months after the last dose of DANYELZA.

8.3 Females and Males of Reproductive Potential

DANYELZA may cause fetal harm when administered to a pregnant woman [see Use in Specific Populations (8.1)].

Pregnancy Testing

Verify pregnancy status in females of reproductive potential prior to initiating DANYELZA.

Contraception

Females

Advise females of reproductive potential to use effective contraception during treatment and for 2 months after the last dose of DANYELZA.

8.4 Pediatric Use

The safety and effectiveness of DANYELZA, in combination with GM-CSF for the treatment of relapsed or refractory high-risk neuroblastoma in the bone or bone marrow who have demonstrated a partial response, minor response or stable disease following prior therapy, have been established in pediatric patients 1 year of age and older.

Safety and effectiveness have not been established in pediatric patients younger than 1 year of age.

8.5 Geriatric Use

Neuroblastoma is largely a disease of pediatric and young adult patients. Clinical studies of DANYELZA in combination with GM-CSF did not include patients 65 years of age and older.

11 DESCRIPTION

Naxitamab-gqgk is a glycolipid disialoganglioside (GD2)-binding recombinant humanized monoclonal IgG1 antibody, that contains human framework regions and murine complementarity-determining regions. Naxitamab-gqgk is produced in a Chinese hamster ovary cell line and has an approximate molecular weight of 144 kDa without glycosylation.

DANYELZA (naxitamab-gqgk) injection is a sterile, preservative-free, clear to slightly opalescent and colorless to slightly yellow solution for intravenous infusion. Each single-dose vial contains 40 mg of naxitamab-gqgk in 10 mL of solution. Each mL of solution contains 4 mg of naxitamab-gqgk, and citric acid anhydrous (0.71 mg), poloxamer 188 (1.5 mg), sodium chloride (7.01 mg), sodium citrate (6.3 mg), and Water for Injection, USP. The pH is approximately 5.7.

12 CLINICAL PHARMACOLOGY

12.1 Mechanism of Action

Naxitamab-gqgk binds to the glycolipid GD2. GD2 is a disialoganglioside that is overexpressed on neuroblastoma cells and other cells of neuroectodermal origin, including the central nervous system and peripheral nerves. In vitro, naxitamab-gqgk was able to bind to cell surface GD2 and induce complement dependent cytotoxicity (CDC) and antibody dependent cell-mediated cytotoxicity (ADCC).

12.2 Pharmacodynamics

The exposure-response relationship and time course of pharmacodynamic response for the safety and effectiveness of naxitamab-gqgk have not been fully characterized.

12.3 Pharmacokinetics

The geometric mean (CV%) maximum plasma concentration (Cmax) of naxitamab-gqgk was 57.4 µg/mL (49%) following DANYELZA 3 mg/kg intravenous infusion over 30 minutes.

Elimination

The mean terminal half-life of naxitamab-gqgk was 8.2 days.

Metabolism

Naxitamab-gqgk is expected to be metabolized into small peptides by catabolic pathways.

Specific Populations

Population pharmacokinetic analyses suggest that age (range: 1 to 34 years), sex and race have no clinically important effect on the clearance (CL) of naxitamab-gqgk. The naxitamab-gqgk systemic exposure (AUC) at 150 mg/day (450 mg per cycle) for patients with body weight over 50 kg is not expected to differ clinically from that of the naxitamab-gqgk exposures at 3 mg/kg/day (9 mg/kg per cycle) for patients with body weight of 30 - 50 kg.

13 NONCLINICAL TOXICOLOGY

13.1 Carcinogenesis, Mutagenesis, Impairment of Fertility

No animal studies have been conducted to evaluate the carcinogenic or mutagenic potential of naxitamab-gqgk.

Dedicated studies evaluating the effects of naxitamab-gqgk on fertility in animals have not been conducted.

13.2 Animal Toxicology and/or Pharmacology

Non-clinical studies suggest that naxitamab-gqgk-induced neuropathic pain is mediated by binding of the antibody to the GD2 antigen located on the surface of peripheral nerve fibers and myelin and subsequent induction of immune-mediated cytotoxic activity.

In a nude rat model, slight-moderate hyperplasia and erosion of the glandular mucosa of the stomach occurred, occasionally accompanied by diffuse inflammation. Complete recovery of all histopathological findings in the stomachs of male rats was observed; however, only partial recovery was observed in the stomachs of female rats during the four week off-drug period.

14 CLINICAL STUDIES

The efficacy of DANYELZA in combination with GM-CSF was evaluated in two open-label, single arm trials in patients with high-risk neuroblastoma with refractory or relapsed disease in the bone or bone marrow, Study 201 and Study 12-230.

Study 201

The efficacy of DANYELZA in combination with GM-CSF was evaluated in Study 201 (NCT03363373), a multicenter open-label, single arm trial, in a subpopulation of patients who had refractory or relapsed high-risk neuroblastoma in the bone or bone marrow and demonstrated a partial response, minor response, or stable disease to prior therapy. Patients with progressive disease were excluded. All patients received at least one systemic therapy to treat disease outside of the bone or bone marrow prior to enrollment. Patients received DANYELZA 9 mg/kg/cycle administered as three separate intravenous infusions of 3 mg/kg on Days 1, 3 and 5 of each cycle. Patients received GM-CSF subcutaneously at 250 µg/m^2/day on Days -4 to 0 and at 500 µg/m^2/day on Days 1 to 5. Preplanned radiation to the primary site was allowed.

The major efficacy outcome measure was overall response rate (ORR) according to the revised International Neuroblastoma Response Criteria (INRC), as determined by independent pathology and imaging review and confirmed by at least one subsequent assessment. An additional efficacy outcome measure was duration of response (DOR).

Of the 22 patients included in the efficacy analysis, 64% had refractory disease and 36% had relapsed disease; the median age was 5 years (range 3 to 10 years), 59% were male; 45% were White, 50% were Asian and 5% were Black. MYCN amplification was present in 14% of patients and 86% of patients were International Neuroblastoma Staging System (INSS) stage 4 at time of diagnosis. Disease sites included 59% in the bone only, 9% in bone marrow only, and 32% in both. Prior therapies included surgery (91%), chemotherapy (95%), radiation (36%), autologous stem cell transplant (ASCT) (18%), and anti-GD2 antibody treatment (18%).

Efficacy results for Study 201 are described in Table 8.

Table 8. Efficacy Results from Study 201
 | DANYELZA with GM-CSF (n=22)
Overall response rate [Overall response rate is defined as a complete or partial response according to the revised INRC (2017) that was confirmed by at least one subsequent assessment. Responses were observed in the bone, bone marrow, or both bone and bone marrow.] (95% CI) | 45% (24%, 68%)
Complete response rate | 36%
Partial response rate | 9%
Duration of response
Median (95% CI), months | 6.2 (4.9, NE)
Responders with DOR ≥ 6 months | 30%
CI = confidence interval
NE: not estimable.

In an exploratory analysis in the subset of patients previously treated with an anti-GD2 antibody (n=4), one patient demonstrated a confirmed complete response and no patients demonstrated a partial response.

Study 12-230

The efficacy of DANYELZA in combination with GM-CSF was evaluated in Study 12-230 (NCT01757626), a single center, open-label, single arm trial, in a subpopulation of patients who had relapsed or refractory high-risk neuroblastoma in bone or bone marrow and demonstrated a partial response, minor response, or stable disease to prior therapy. Patients with progressive disease were excluded. All patients received at least one systemic therapy to treat disease outside of the bone or bone marrow prior to enrollment. Patients were required to have received at least one dose of DANYELZA at a dose of 3 mg/kg or greater per infusion and have evaluable disease at baseline according to independent review per the revised INRC.

Patients received DANYELZA 9 mg/kg/cycle administered as three separate intravenous infusions of 3 mg/kg (on Days 1, 3 and 5) in the first week of each cycle. Patients received GM-CSF subcutaneously at 250 µg/m^2/day on Days -4 to 0 and at 500 µg/m^2/day on Days 1 to 5. Radiation to non-target bony lesions and soft tissue lesions was permitted at the investigator's discretion; assessment of response excluded sites that received radiation. The major efficacy outcome measures were overall response rate (ORR) and duration of response (DOR), as determined by independent pathology and imaging review according to the revised INRC and confirmed by at least one subsequent assessment.

Of the 38 patients included in the efficacy analysis, 55% had relapsed neuroblastoma and 45% had refractory disease; 50% were male, the median age was 5 years (range 2 to 23 years), 74% were White, 8% Asian and 5% were Black, 5% Native American/American Indian/Alaska Native, 3% other races and 5% was not available. MYCN-amplification was present in 16% of patients and most patients were International Neuroblastoma Staging System (INSS) stage 4 (95%). Fifty percent (50%) of patients had disease involvement in the bone only, 11% only in bone marrow, and 39% in both. Prior therapies included surgery (100%), chemotherapy (100%), radiation (47%), autologous stem cell transplant (ASCT) (42%), and anti-GD2 antibody treatment (58%).

Efficacy results are provided in Table 9.

Table 9. Efficacy Results from Study 12-230
 | DANYELZA with GM-CSF (n=38)
Overall response rate [Overall response rate is defined as a complete or partial response according to the revised INRC (2017) that was confirmed by at least one subsequent assessment. Responses were observed in the bone, bone marrow, or both bone and bone marrow.] (95% CI) | 34% (20%, 51%)
Complete response rate | 26%
Partial response rate | 8%
Duration of Response
Responders with DOR ≥ 6 months | 23%
CI = confidence interval

In an exploratory analysis in the subset of patients previously treated with an anti-GD2 antibody (n=22), the ORR was 18% (95% CI 5%, 40%), with no patients having a documented response of 6 months or greater.

16 HOW SUPPLIED / STORAGE AND HANDLING

DANYELZA (naxitamab-gqgk) injection is a sterile, preservative-free, clear to slightly opalescent and colorless to slightly yellow solution for intravenous infusion supplied as a carton containing one 40mg/10 mL (4 mg/mL) single-dose vial.

NDC 73042-201-01

STORAGE AND HANDLING

Store DANYELZA vial refrigerated at 2°C to 8°C (36°F to 46°F) in the outer carton to protect from light until time of use.

17 PATIENT COUNSELING INFORMATION

Advise the patient and caregiver to read the FDA-approved patient labeling (Patient Information).

Serious Infusion-Related Reactions

Advise patients and caregivers that DANYELZA can cause serious infusion-related reactions and anaphylaxis and to immediately report any signs or symptoms, such as facial or lip swelling, urticaria, or difficulty breathing, that occur during or following the infusion [see Warnings and Precautions (5.1)].

Neurotoxicity

Advise patients and caregivers that DANYELZA can cause neurotoxicity, including severe pain, peripheral neuropathy, neurological disorders of the eye, prolonged urinary retention, transverse myelitis, and reverse posterior leukoencephalopathy syndrome. Advise patients to contact their healthcare provider for any new or worsening neurological symptoms [see Warnings and Precautions (5.2)].

Myocarditis

Advise patients and caregivers that myocarditis has been seen in patients taking DANYELZA and to report any signs or symptoms, such as chest pain, shortness of breath or abnormal heart rhythms during treatment with DANYELZA [see Warnings and Precautions (5.3)].

Hypertension

Advise patients and caregivers that DANYELZA can cause hypertension and to immediately report signs or symptoms of hypertension [see Warnings and Precautions (5.4)].

Orthostatic Hypotension

Advise patients and caregivers that DANYELZA can cause severe low blood pressure when standing after sitting or lying down. Advise patients and caregivers to report any signs or symptoms, such as dizziness, lightheadedness or fainting during treatment with DANYELZA [see Warnings and Precautions (5.5)].

Embryo-Fetal Toxicity [see Warnings and Precautions (5.6) and Use in Specific Populations (8.1, 8.3)].

Advise females of reproductive potential, including pregnant women, of the potential risk to the fetus.

Advise females of reproductive potential to inform their healthcare provider of a known or suspected pregnancy and to use effective contraception during treatment with and for 2 months after the last dose of DANYELZA.

Lactation

Advise women not to breastfeed during treatment with DANYELZA and for 2 months after the last dose [see Use in Specific Populations (8.2)].

DANYELZA® is a registered trademark of Y-mAbs Therapeutics, Inc.

© 2025 Y-mAbs Therapeutics, Inc. – All rights reserved.

Manufactured by:
Y-mAbs Therapeutics, Inc
202 Carnegie Center, Suite 301
Princeton, NJ 08540
U.S. License No. 2209

PATIENT INFORMATION
DANYELZA® (dan-YEL-zah)
(naxitamab-gqgk)
injection, for intravenous use

What is the most important information I should know about DANYELZA?
DANYELZA may cause serious side effects, including:

- Serious infusion-related reactions. DANYELZA can cause serious infusion-related reactions that require immediate medical attention. Infusion-related reactions are common with DANYELZA. Tell your healthcare provider right away if you get any signs or symptoms during or after your DANYELZA infusion, including:

- swelling of your face, eyes, lips, mouth, or tongue
- itching
- redness on your face (flushing)
- skin rash or hives

- trouble breathing
- cough or wheezing
- noisy high-pitched breathing
- feeling faint or dizziness (low blood pressure)

- Nervous system problems. Talk to your healthcare provider right away if you have new symptoms or worsening of nervous system problems, including:

- Severe pain from nerves (neuropathic pain), including pain in the belly (abdomen), bone, neck, legs or arms. Pain is common with DANYELZA and can be severe.
- Inflammation of the spinal cord. Signs or symptoms may include:

- weakness in your legs or arms
- bladder and bowel problems
- pain in back, legs, or stomach (abdomen)

- numbness
- tingling
- burning sensation

- Reversible Posterior Leukoencephalopathy Syndrome (RPLS – also known as Posterior Reversible Encephalopathy Syndrome - PRES). PRES is a condition that affects the brain. Your healthcare provider will monitor your blood pressure and check for any neurologic symptoms after your DANYELZA infusion. Signs or symptoms of PRES may include:

- severe headache
- vision changes
- changes in mental status, such as confusion, disorientation, or decreased alertness

- difficulty speaking
- weakness in your arms or legs
- seizures

- Numbness, tingling, or burning sensation in the arms or legs.
- Nervous system problems of the eye. Signs or symptoms may include:

- unequal pupil size
- blurred vision
- trouble focusing your eyes

- larger pupil size (dilated)
- decreased ability to see
- sensitivity to light

- Problems urinating or emptying your bladder (prolonged urinary retention).

What is DANYELZA?
DANYELZA is a prescription medicine used in combination with a medicine called granulocyte-macrophage colony-stimulating factor (GM-CSF) to treat children 1 year of age and older and adults with high-risk neuroblastoma in the bone or bone marrow that:

- has come back (relapsed) or that did not respond to previous treatment (refractory), and
- has shown a partial response, minor response, or stable disease to prior therapy.

It is not known if DANYELZA is safe and effective in children younger than 1 year of age.

Do not receive DANYELZA if you have had a severe allergic reaction to naxitamab-gqgk, the active ingredient in DANYELZA. Ask your healthcare provider if you are not sure.

Before receiving DANYELZA, tell your healthcare provider about all your medical conditions, including if you:

- have high blood pressure
- have heart disease
- are pregnant or plan to become pregnant. DANYELZA may harm your unborn baby.

- Your healthcare provider will do a pregnancy test before you start treatment with DANYELZA.
- Females who are able to become pregnant should use effective birth control (contraception) during treatment and for 2 months after your last dose of DANYELZA. Talk to your healthcare provider about birth control choices that may be right for you during this time.
- Tell your healthcare provider right away if you become pregnant or think you might be pregnant during treatment with DANYELZA.

- are breastfeeding or plan to breastfeed. It is not known if DANYELZA passes into your breast milk. Do not breastfeed during treatment and for 2 months after your last dose of DANYELZA.

Tell your healthcare provider about all the medicines you take, including prescription and over-the-counter medicines, vitamins, and herbal supplements.

How will I receive DANYELZA?

- Your healthcare provider will give you DANYELZA into your vein through an intravenous (I.V.) line over 30 or 60 minutes.
- DANYELZA is given on Days 1, 3, and 5 of each treatment cycle.
- DANYELZA is used with another medicine called GM-CSF. You can ask your healthcare provider for information about GM-CSF.
- DANYELZA treatment cycles are usually repeated every 4 or 8 weeks. Your healthcare provider will decide how many treatment cycles you need.
- Your healthcare provider will give you certain medicines before and during your DANYELZA infusion to help decrease your risk of getting pain, infusion-related reactions, and nausea or vomiting.
- Your healthcare provider may slow down your infusion rate, temporarily stop DANYELZA infusion, or permanently stop treatment with DANYELZA if you have certain side effects.
- You will be monitored for side effects for at least 2 hours after each DANYELZA infusion.
- If you miss an appointment, call your healthcare provider as soon as possible to reschedule.

What are the possible side effects of DANYELZA?
DANYELZA may cause serious side effects, including:

- See "What is the most important information I should know about DANYELZA?"
- Swelling of the heart (myocarditis). Myocarditis has happened in adolescents ages 12 to 18 within days of receiving DANYELZA. Tell your healthcare provider if you get any signs or symptoms of myocarditis, including:

- chest pain
- shortness of breath

- irregular heartbeat or feel like your heart is racing

- High blood pressure (hypertension). High blood pressure is common in people who receive DANYELZA. Your blood pressure will be monitored during your DANYELZA infusion, and at least each day on Days 1 to 8 of each DANYELZA treatment cycle. Tell your healthcare provider right away if you get any signs or symptoms of high blood pressure, including:

- headaches
- seizures
- nausea or vomiting
- chest pain
- dizziness

- visual changes
- shortness of breath
- feeling that your heart is pounding or racing (palpitations)
- nose bleeds

- Decreased blood pressure (orthostatic hypotension) that can be severe and require hospitalization. You may feel dizzy, lightheaded, or pass out (faint) when you rise too quickly from a sitting or lying position. Your healthcare provider will monitor your blood pressure before you start and during treatment with DANYELZA.

The most common side effects of DANYELZA include:

- fast heart rate
- vomiting
- cough
- nausea
- decreased white blood cell, red blood cell, and platelet counts
- diarrhea
- decreased appetite
- tiredness
- skin rashes

- decreased level of potassium, sodium, and phosphate in the blood
- hives
- fever
- headache
- injection site reaction
- swelling of the body or only in one part of the body
- anxiety

- irritability
- increased liver function blood tests
- decreased blood sugar level
- decreased calcium levels in the blood
- decreased protein levels (albumin) in the blood

These are not all of the possible side effects of DANYELZA.
Call your doctor for medical advice about side effects. You may report side effects to FDA at 1-800-FDA-1088.

General information about the safe and effective use of DANYELZA.
Medicines are sometimes prescribed for purposes other than those listed in a Patient Information leaflet. You can ask your pharmacist or healthcare provider for information about DANYELZA that is written for health professionals.

What are the ingredients in DANYELZA?
Active ingredient: naxitamab-gqgk
Inactive ingredients: citric acid anhydrous, poloxamer 188, sodium chloride, sodium citrate, Water for Injection.
Manufactured by: Y-mAbs Therapeutics, Inc., 202 Carnegie Center, Suite 301, Princeton, NJ 08540
U.S. License number 2209
For more information, go to www.DANYELZA.com or call 1-833-339-6227 (1-833-33YMABS)

This Patient Information has been approved by the U.S. Food and Drug Administration

Revised: 08/2025

PRINCIPAL DISPLAY PANEL - 10 mL Vial Carton

NDC 73042-201-01

DANYELZA®
(naxitamab-gqgk)
Injection

40 mg/10 mL
(4 mg/mL)

Rx ONLY

For intravenous
infusion after dilution

Single-dose vial

Discard unused portion

No preservative

Y-mAbs Therapeutics, Inc.™